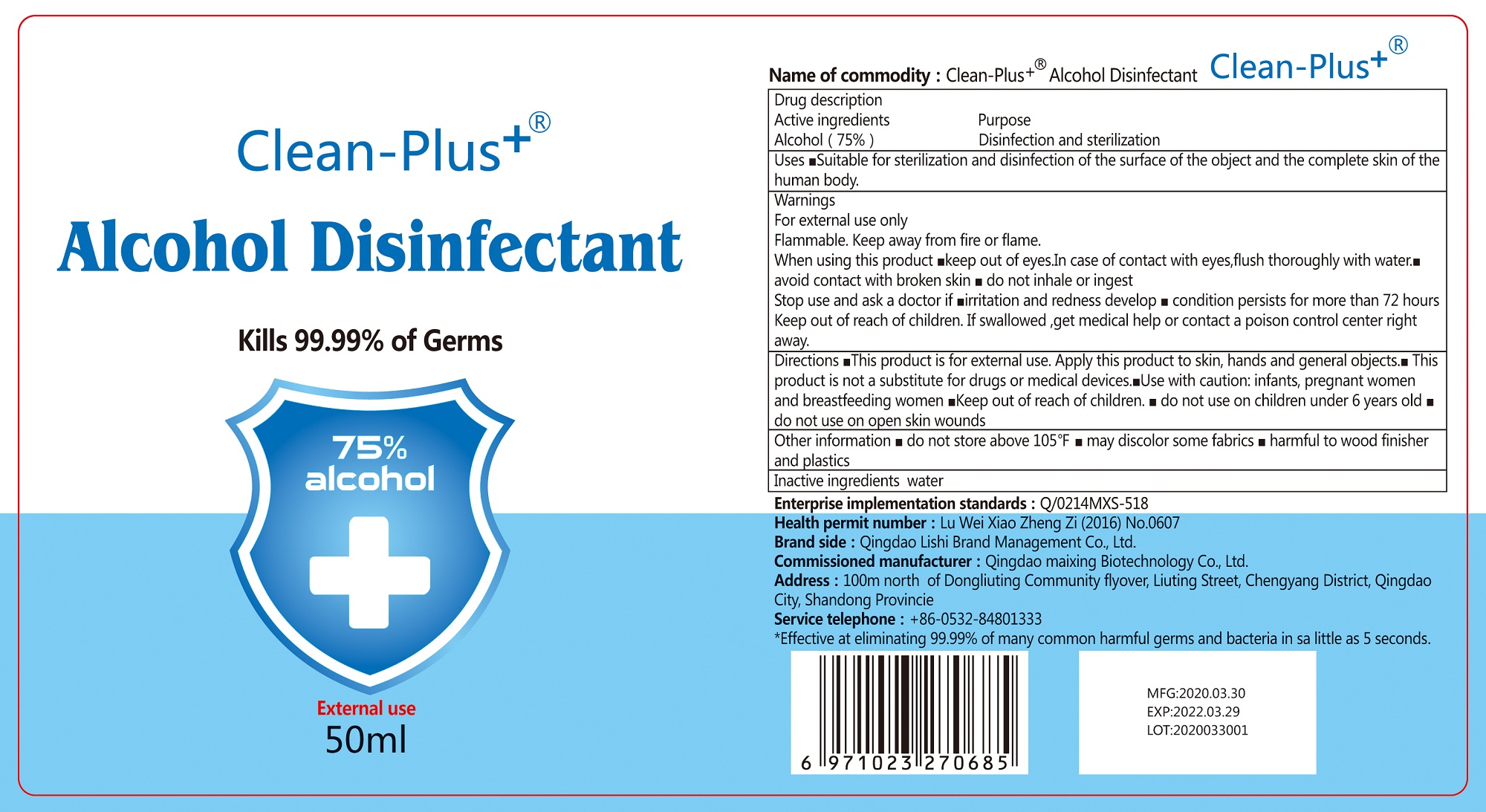 DRUG LABEL: Alcohol Disinfectant
NDC: 75711-003 | Form: LIQUID
Manufacturer: Qingdao Maixing Biotechnology Co.,Ltd
Category: otc | Type: HUMAN OTC DRUG LABEL
Date: 20200422

ACTIVE INGREDIENTS: ALCOHOL 37.5 mL/50 mL
INACTIVE INGREDIENTS: WATER

Hand Sanitizer

This is a hand sanitizer manufactured according to the Temporary Policy for Preparation of Certain Alcohol-Based Hand Sanitizer Products During the Public Health Emergency (CoViD-19); Guidance for Industry.

The hand sanitizer is manufactured using only the following United States Pharmacopoeia (USP) grade ingredients in the preparation of the product (percentage in final product formulation) consistent with World Health Organization (WHO) recommendations:

1. Alcohol (ethanol) (USP or Food Chemical Codex (FCC) grade) (75%, volume/volume (v/v)) in an aqueous solution denatured according to Alcohol and Tobacco Tax and Trade Bureau regulations in 27 CFR part 20.
2. Sterile distilled water or boiled cold water.

The firm does not add other active or inactive ingredients. Different or additional ingredients may impact the quality and potency of the product.

Active Ingredient(s)

Alcohol 75% v/v. Purpose: disinfection and antiseptic

Purpose

Antiseptic, Hand Sanitizer

purpose:disinfection and antiseptic

Use

Suitable for sterilization and disinfection of the surface of the object and the complete skin of the human body.

Warnings

For external use only. Flammable. Keep away from heat or flame

- do not use on children 6 years old.
- do not use on open skin wounds

WHEN USING

Keep out of eyes.in case of contact with eyes,flush thoroughly with water.

Avoid contact with broken skin.

Do not inhale or ingest.

stop use and ask a doctor if irritation and redness develop,condition persists for more tahn 72 hours

Keep out of reach of children. If swallowed, get medical help or contact a poison control center right away.

Directions

this product is for extermal use.apply this product to skin,hands and general objects
this product is not a substitute for drugs or medical devices
use with caution;infants, pregnant women and breastfeeding women
keep out of reach of children,
do not use on children 6 years old.do not use on open skin wounds

Other information

- do not store above 105.F
- may discolor some fabrics
- harmful to wood finisher and plastics

Inactive ingredients

water

Package Label - Principal Display Panel

50 mL NDC: